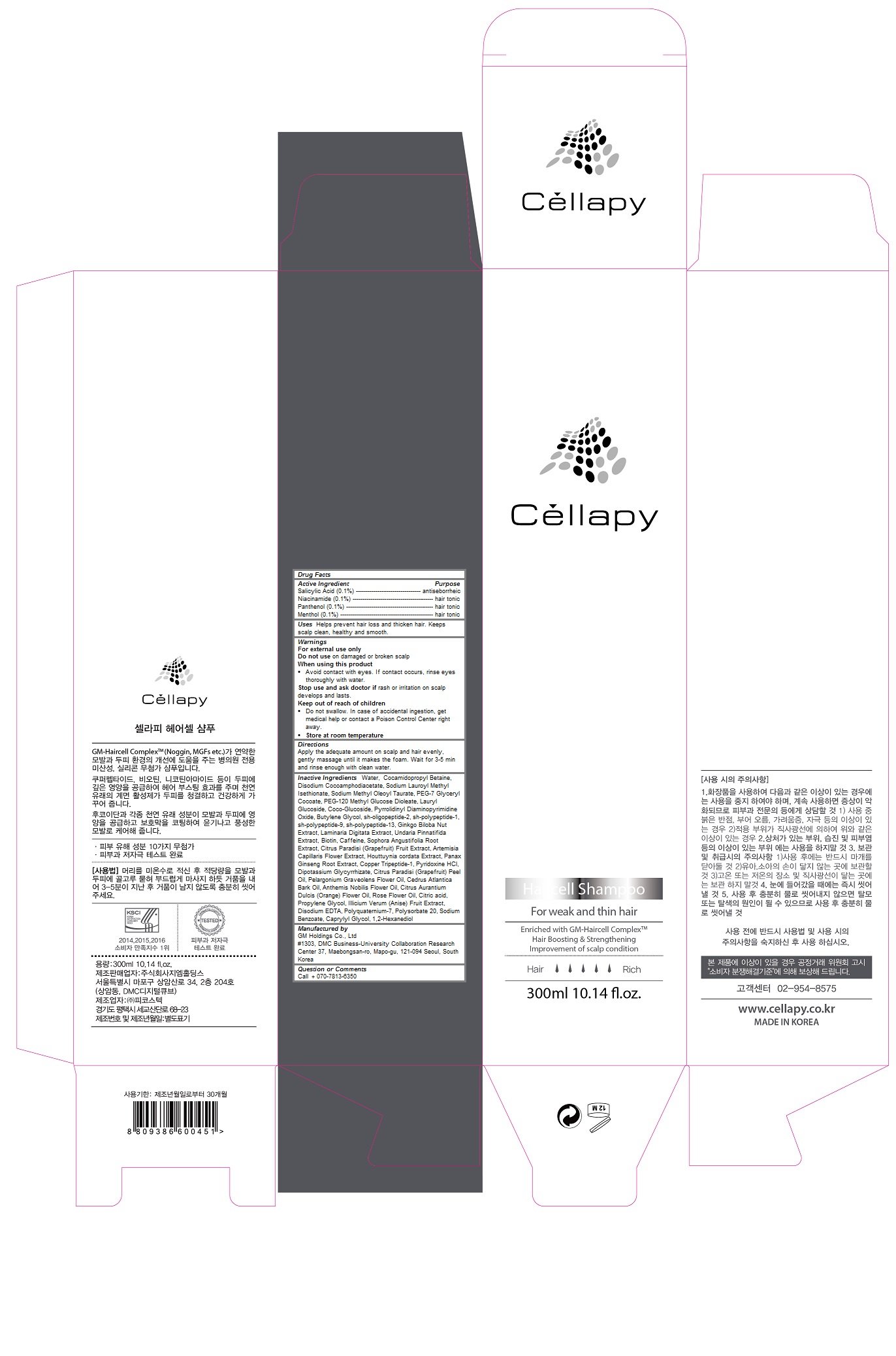 DRUG LABEL: Cellapy Haircell
NDC: 69278-107 | Form: SHAMPOO
Manufacturer: Gm Holdings Co., Ltd
Category: otc | Type: HUMAN OTC DRUG LABEL
Date: 20200121

ACTIVE INGREDIENTS: SALICYLIC ACID 0.001 1/300 mL; NIACINAMIDE 0.001 1/300 mL; PANTHENOL 0.001 1/300 mL; MENTHOL 0.001 1/300 mL
INACTIVE INGREDIENTS: WATER; COCAMIDOPROPYL BETAINE; DISODIUM COCOAMPHODIACETATE; SODIUM LAUROYL METHYL ISETHIONATE; SODIUM METHYL OLEOYL TAURATE; PEG-7 GLYCERYL COCOATE; PEG-120 METHYL GLUCOSE DIOLEATE; LAURYL GLUCOSIDE; COCO GLUCOSIDE; PYRROLIDINYL DIAMINOPYRIMIDINE OXIDE; BUTYLENE GLYCOL; MECASERMIN; BASIC FIBROBLAST GROWTH FACTOR (HUMAN); HUMAN NOGGIN; GINKGO BILOBA SEED; LAMINARIA DIGITATA; UNDARIA PINNATIFIDA; BIOTIN; CAFFEINE; SOPHORA FLAVESCENS ROOT; GRAPEFRUIT; ARTEMISIA CAPILLARIS FLOWER; HOUTTUYNIA CORDATA FLOWERING TOP; ASIAN GINSENG; PREZATIDE COPPER; PYRIDOXINE HYDROCHLORIDE; GLYCYRRHIZINATE DIPOTASSIUM; GRAPEFRUIT OIL; PELARGONIUM GRAVEOLENS FLOWER OIL; CEDRUS ATLANTICA BARK OIL; CHAMAEMELUM NOBILE FLOWER OIL; CITRUS SINENSIS FLOWER OIL; CITRIC ACID MONOHYDRATE; PROPYLENE GLYCOL; STAR ANISE FRUIT; EDETATE DISODIUM; POLYSORBATE 20; SODIUM BENZOATE; CAPRYLYL GLYCOL; 1,2-HEXANEDIOL

Cellapy Haircell Shampoo